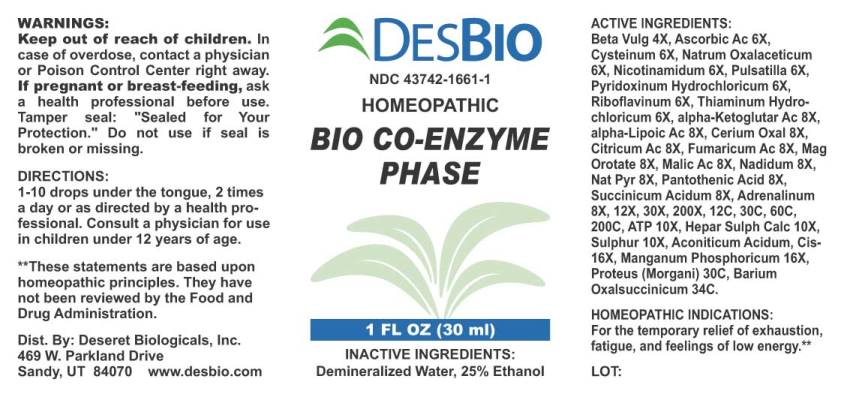 DRUG LABEL: Bio Co-Enzyme Phase
NDC: 43742-1661 | Form: LIQUID
Manufacturer: Deseret Biologicals, Inc.
Category: homeopathic | Type: HUMAN OTC DRUG LABEL
Date: 20220509

ACTIVE INGREDIENTS: BETA VULGARIS WHOLE 4 [hp_X]/1 mL; ASCORBIC ACID 6 [hp_X]/1 mL; CYSTEINE 6 [hp_X]/1 mL; SODIUM DIETHYL OXALACETATE 6 [hp_X]/1 mL; NIACINAMIDE 6 [hp_X]/1 mL; PULSATILLA PRATENSIS WHOLE 6 [hp_X]/1 mL; PYRIDOXINE HYDROCHLORIDE 6 [hp_X]/1 mL; RIBOFLAVIN 6 [hp_X]/1 mL; THIAMINE HYDROCHLORIDE 6 [hp_X]/1 mL; OXOGLURIC ACID 8 [hp_X]/1 mL; ALPHA LIPOIC ACID 8 [hp_X]/1 mL; CEROUS OXALATE NONAHYDRATE 8 [hp_X]/1 mL; ANHYDROUS CITRIC ACID 8 [hp_X]/1 mL; FUMARIC ACID 8 [hp_X]/1 mL; MAGNESIUM OROTATE DIHYDRATE 8 [hp_X]/1 mL; MALIC ACID 8 [hp_X]/1 mL; NADIDE 8 [hp_X]/1 mL; SODIUM PYRUVATE 8 [hp_X]/1 mL; PANTOTHENIC ACID 8 [hp_X]/1 mL; SUCCINIC ACID 8 [hp_X]/1 mL; EPINEPHRINE 8 [hp_X]/1 mL; ADENOSINE TRIPHOSPHATE DISODIUM 10 [hp_X]/1 mL; CALCIUM SULFIDE 10 [hp_X]/1 mL; SULFUR 10 [hp_X]/1 mL; ACETIC ACID 16 [hp_X]/1 mL; MANGANESE PHOSPHATE, DIBASIC 16 [hp_X]/1 mL; PROTEUS MORGANII 30 [hp_C]/1 mL; BARIUM OXALOSUCCINATE 34 [hp_C]/1 mL
INACTIVE INGREDIENTS: WATER; ALCOHOL

Drug Facts:

ACTIVE INGREDIENTS:

Beta Vulgaris 4X, Ascorbicum Acidum 6X, Cysteinum 6X, Natrum Oxalaceticum 6X, Nicotinamidum 6X, Pulsatilla (Pratensis) 6X, Pyridoxinum Hydrochloricum 6X, Riboflavinum 6X, Thiaminum Hydrochloricum 6X, Alpha-Ketoglutaricum Acidum 8X, Alpha-Lipoicum Acidum 8X, Cerium Oxalicum 8X, Citricum Acidum 8X, Fumaricum Acidum 8X, Magnesium Oroticum Dihydricum 8X, Malicum Acidum 8X, Nadidum 8X, Natrum Pyruvicum 8X, Pantothenic Acid 8X, Succinicum Acidum 8X, Adrenalinum 8X, 12X, 30X, 200X, 12C, 30C, 60C, 200C, Adenosinum Triphosphoricum Dinatrum 10X, Hepar Sulphuris Calcareum 10X, Sulphur 10X, Aconiticum Acidum, Cis 16X, Manganum Phosphoricum 16X, Proteus (Morgani) 30C, Barium Oxalsuccinicum 34C.

HOMEOPATHIC INDICATIONS:

For the temporary relief of exhaustion, fatigue, and feelings of low energy.**

**These statements are based upon homeopathic principles. They have not been reviewed by the Food and Drug Administration.

WARNINGS:

Keep out of reach of children. In case of overdose, contact a physician or Poison Control Center right away.

If pregnant or breast-feeding, ask a health professional before use.

Tamper seal: "Sealed for Your Protection." Do not use if seal is broken or missing.

Keep out of reach of children. In case of overdose, contact a physician or Poison Control Center right away.

DIRECTIONS:

1-10 drops under the tongue, 2 times a day or as directed by a health professional. Consult a physician for use in children under 12 years of age.

HOMEOPATHIC INDICATIONS:

For the temporary relief of exhaustion, fatigue, and feelings of low energy.**

**These statements are based upon homeopathic principles. They have not been reviewed by the Food and Drug Administration.

INACTIVE INGREDIENTS:

Demineralized Water, 25% Ethanol

QUESTIONS:

Dist. By: Deseret Biologicals, Inc.

469 W. Parkland Drive

Sandy, UT 84070 www.desbio.com

PACKAGE LABEL DISPLAY:

DESBIO
NDC 43742-1661-1
HOMEOPATHIC
BIO CO-ENZYME PHASE
1 FL OZ (30 ml)